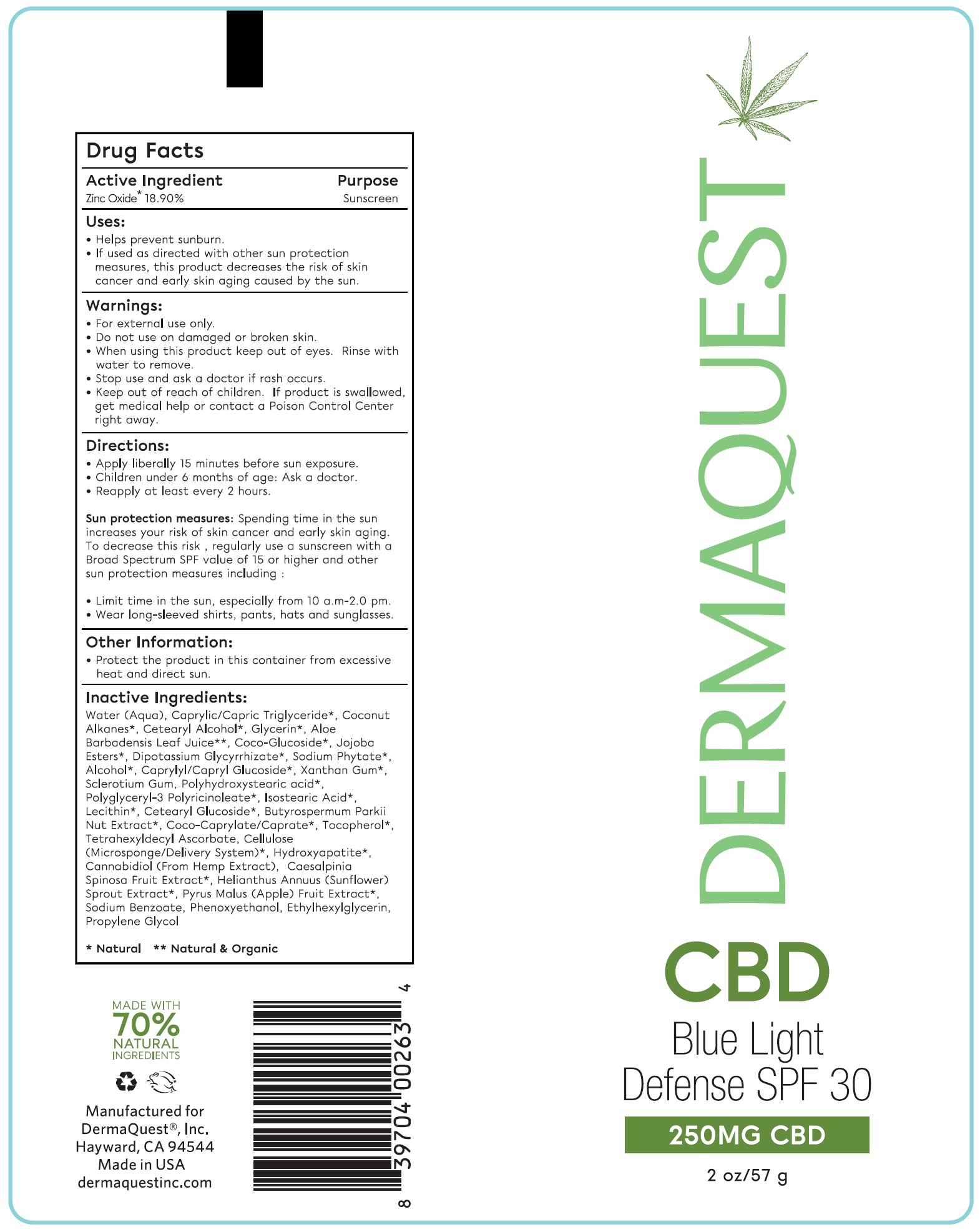 DRUG LABEL: CBD Blue Light Defense SPF 30
NDC: 62742-4196 | Form: CREAM
Manufacturer: Allure Labs
Category: otc | Type: HUMAN OTC DRUG LABEL
Date: 20241205

ACTIVE INGREDIENTS: ZINC OXIDE 189 mg/1 g
INACTIVE INGREDIENTS: TETRAHEXYLDECYL ASCORBATE; TRIBASIC CALCIUM PHOSPHATE; CANNABIDIOL; CAESALPINIA SPINOSA FRUIT POD; APPLE; PHENOXYETHANOL; ETHYLHEXYLGLYCERIN; CETOSTEARYL ALCOHOL; ALOE VERA LEAF; HYDROGENATED JOJOBA OIL, RANDOMIZED; WATER; XANTHAN GUM; POLYHYDROXYSTEARIC ACID (2300 MW); MEDIUM-CHAIN TRIGLYCERIDES; CETEARYL GLUCOSIDE; ISOSTEARIC ACID; SHEANUT; TOCOPHEROL; HELIANTHUS ANNUUS SPROUT; PROPYLENE GLYCOL; SODIUM BENZOATE; COCONUT ALKANES; GLYCERIN; COCO GLUCOSIDE; GLYCYRRHIZINATE DIPOTASSIUM; POLYGLYCERYL-3 PENTARICINOLEATE; PHYTATE SODIUM; ALCOHOL; CAPRYLYL/CAPRYL OLIGOGLUCOSIDE; LECITHIN, SOYBEAN; COCO-CAPRYLATE/CAPRATE; POWDERED CELLULOSE; BETASIZOFIRAN

DRUG FACTS

Active Ingredient

Zinc Oxide 18.90%

Purpose: Sunscreen

Uses:

- Helps prevent sunburn.
- If used as directed with other sun protection measure, this product decreases the risk of skin cancer and early skin aging caused by the sun.

Warnings:

- For External Use Only

Do not use on damaged or broken skin.

Stop use and ask a doctor if rash occurs.

KEEP OUT OF REACH OF CHILDREN

Keep out of reach odf childern. If product is swallowed, get medical help or contact a posion control center right away.

Directions:

- Apply liberally 15 minutes before sun exposure.
- Children under 6 months of age: Ask a doctor
- Reapply at least every 2 hours.

OTHER SAFETY INFORMATION

Sun Protection measures: Spending time in the sun increases your risk of skin cancer and early skin aging. to decrease this risk, regularly use a sunscreen with a Broad Specturm SPF value of 15 or higher and other sun protection measures including:

- Limit time in the sun, especially form 10 a.m. - 2:0 pm
- Wear long sleeved shirts, pants, hats and sunglasses.
- Protect the product in this container form excessive heat and direct sun.

INACTIVE INGREDIENT

Other Ingredients: Water (Aqua), Caprylic/Capric Triglyceride , Coco-Caprylate/Caprate , Cetearyl Alcohol, Glycerin , Aloe Barbadensis Leaf Juice , Coco-Glucoside, Jojoba Esters , Dipotassium Glycyrrhizate , Sodium Phytate, Alcohol, Caprylyl/Capryl Glucoside, Xanthan Gum , Sclerotium Gum, Polyhydroxystearic acid, Polyglyceryl-3 Polyricinoleate, Isostearic Acid, Lecithin, Cetearyl Glucoside, Butyrospermum Parkii Nut Extract , Coconut Alkanes , Tocopherol , Tetrahexyldecyl Ascorbate, Cellulose (Microsponge/Delivery System), Hydroxyapatite, Cannabidiol (From Hemp Extract) , Caesalpinia Spinosa Fruit Extract, Helianthus Annuus (Sunflower) Sprout Extract, Pyrus Malus (Apple) Fruit Extract , Sodium Benzoate, Phenoxyethanol , Ethylhexylglycerin, Propylene Glycol

PACKAGE LABEL

Msanufacture for

Dermaquest®, Inc.

Hayward, CA-94544

Made in USA

dermaquestinc.com